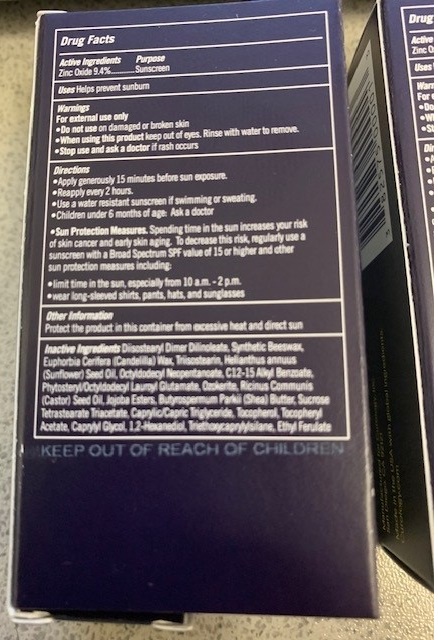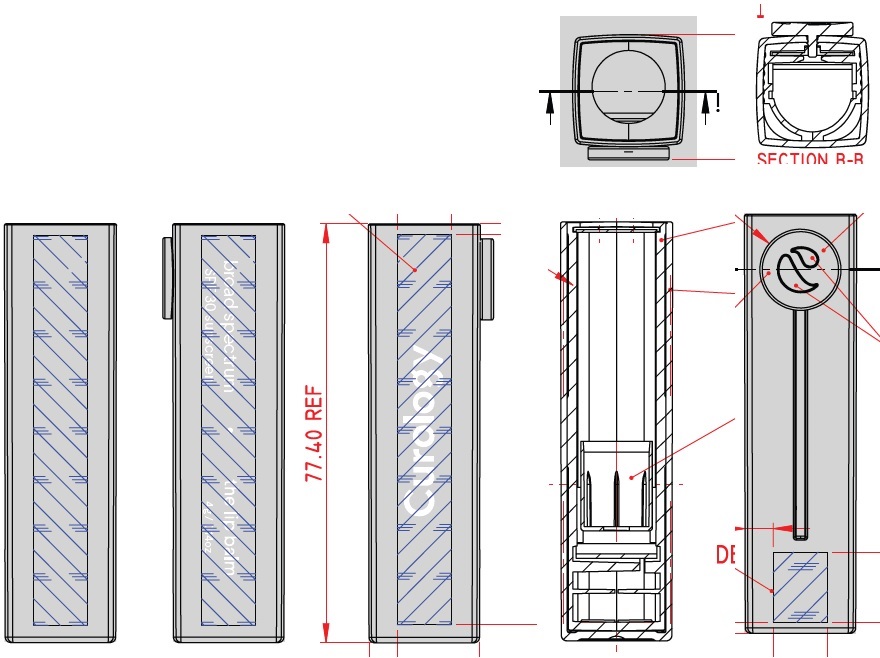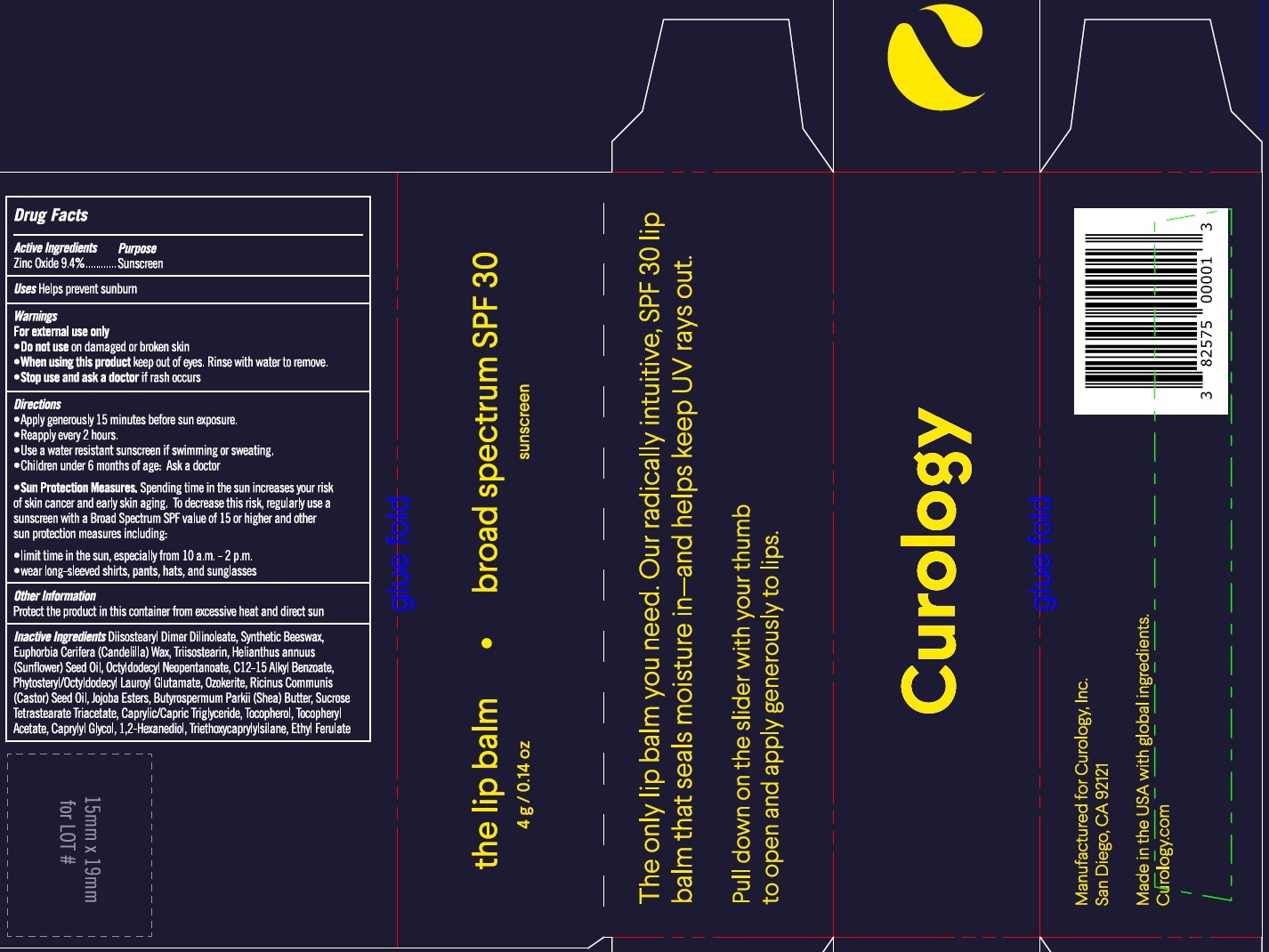 DRUG LABEL: Curology The Lip Balm Broad Spectrum SPF 30 Sunscreen
NDC: 82575-034 | Form: STICK
Manufacturer: Curology Inc.
Category: otc | Type: HUMAN OTC DRUG LABEL
Date: 20251015

ACTIVE INGREDIENTS: ZINC OXIDE 94 mg/1 g
INACTIVE INGREDIENTS: DIISOSTEARYL DIMER DILINOLEATE; SYNTHETIC BEESWAX; CANDELILLA WAX; TRIISOSTEARIN; SUNFLOWER OIL; OCTYLDODECYL NEOPENTANOATE; ALKYL (C12-15) BENZOATE; PHYTOSTERYL/OCTYLDODECYL LAUROYL GLUTAMATE; CASTOR OIL; SHEA BUTTER; SUCROSE TETRASTEARATE TRIACETATE; MEDIUM-CHAIN TRIGLYCERIDES; TOCOPHEROL; .ALPHA.-TOCOPHEROL ACETATE; CAPRYLYL GLYCOL; 1,2-HEXANEDIOL; TRIETHOXYCAPRYLYLSILANE; ETHYL FERULATE

Curology The Lip Balm Broad Spectrum SPF 30 Sunscreen (82575-034)

Active Ingredients

Zinc Oxide 9.4%

Purpose

Sunscreen

Uses

Helps prevent sunburn

Warnings

For external use only

Do not use

- on damaged or broken skin

When using this product

- keep out of eyes. Rinse with water to remove.

Stop use and ask a doctor

if rash occurs

Directions

- Apply generously 15 minutes before sun exposure.
- Reapply every 2 hours.
- Use a water resistant sunscreen if swimming or sweating.
- Children undre 6 months of age: Ask a doctor
- Spending time in the sun increases your risk of skin cancer and early skin aging. To decrease this risk, regularly use a sunscreen with a Broad Spectrum SPF value of 15 or higher and other sun protection measures including: Sun Protection Measures.
- limit time in the sun, especially from 10 a.m.-2 p.m.
- wear long-sleeved shirts, pants, hats, and sunglasses

Other Information

Protect the product in this container from excessive heat and direct sun

Inactive Ingredients

Diisostearyl Dimer Dilinoleate, Synthetic Beeswax, Euphorbia Cerifera (Candelilla) Wax, Triisostearin, Helianthus Annuus (Sunflower) Seed Oil, Octyldodecyl Neopentanoate, C12-15 Alkyl Benzoate, Phytosteryl/Octyldodecyl Lauroyl Glutamate, Ozokerite, Ricinus Communis (Castor) Seed Oil, Jojoba Esters, Butyrospermum Parkii (Shea) Butter, Sucrose Tetrastearate Triacetate, Caprylic/Capric Triglyceride, Tocopherol, Tocopheryl Acetate, Caprylyl Glycol, 1,2-Hexanediol, Triethoxycaprylylsilane, Ethyl Ferulate